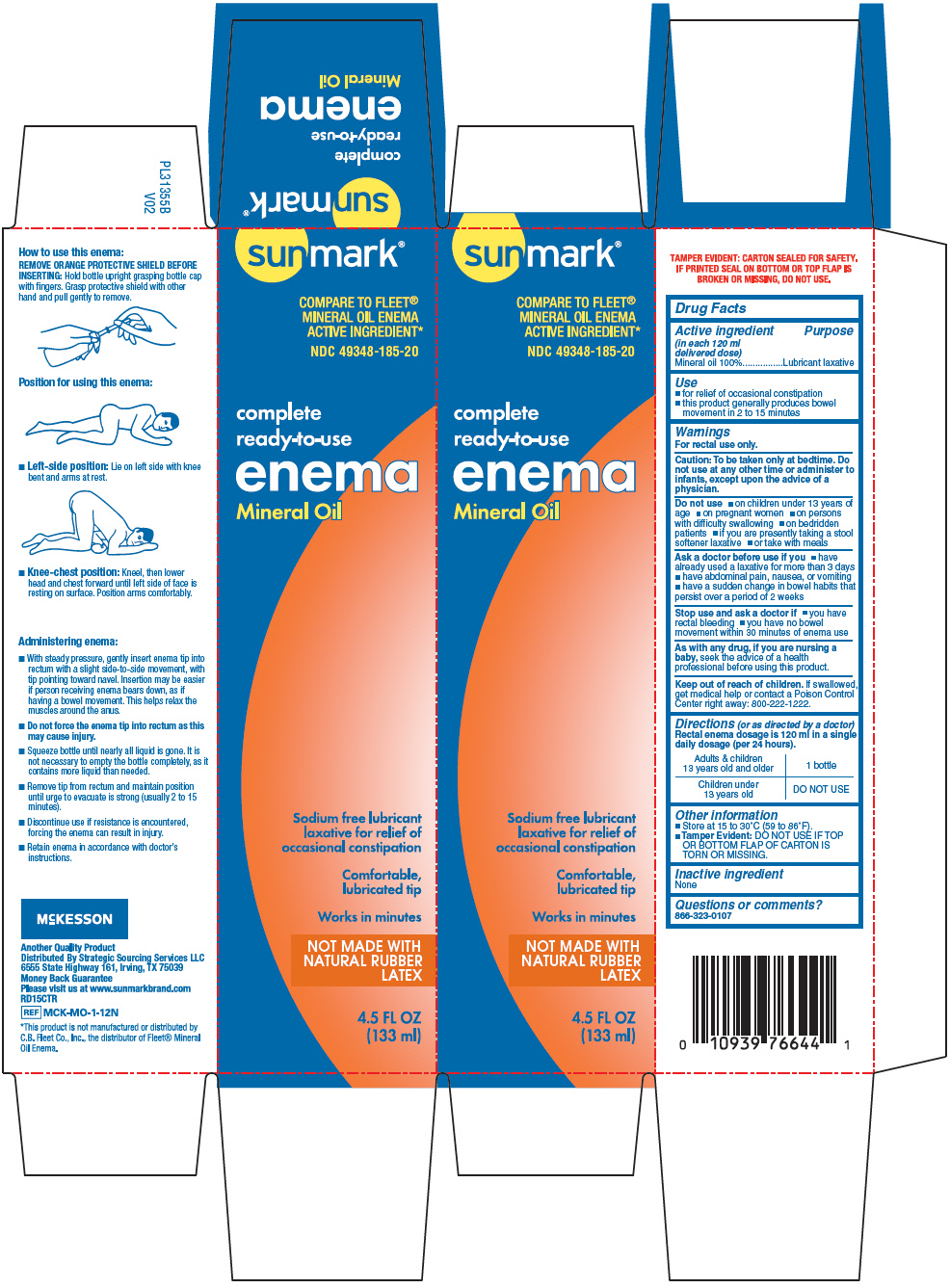 DRUG LABEL: Sunmark Mineral Oil
NDC: 49348-185 | Form: ENEMA
Manufacturer: Strategic Sourcing Services
Category: otc | Type: HUMAN OTC DRUG LABEL
Date: 20250114

ACTIVE INGREDIENTS: Mineral Oil 118 g/118 mL

Sunmark® Mineral Oil Enema
Laxative

Drug Facts

Active ingredient (in each 118 mL delivered dose)

Mineral Oil 100%

Purpose

Lubricant laxative

Use

- for relief of occasional constipation

Warnings

For rectal use only.

Ask a doctor before use if you have

- abdominal pain, nausea, or vomiting
- a sudden change in bowel habits lasting more than 2 weeks
- already used a laxative for more than 1 week

Stop use and ask a doctor if you have:

- rectal bleeding
- no bowel movement after use

These symptoms may indicate a serious condition.

PREGNANCY OR BREAST FEEDING

If pregnant or breast-feeding, ask a health professional before use.

Keep out of reach of children.

If swallowed, get medical help or contact a Poison Control Center right away: 800-222-1222.

Directions

Single daily dosage

Do not use more unless directed by a doctor. See Warnings.

Adults and children 12 years old and over | 1 bottle
Children 2 to under 12 years old | 1/2 bottle once daily
Children under 2 years | DO NOT USE

Other information

- store at 15 to 30°C (59 to 86°F)
- this product generally produces a bowel movement in 1-5 minutes
- carton sealed for safety. Do not use if safety seal on top flap of carton is torn or missing.

Inactive ingredients

none

Questions or comments?

866-323-0107 or www.natureplex.com

Distributed By Strategic Sourcing Services LLC
6555 State Highway 161, Irwing, TX 75039

PRINCIPAL DISPLAY PANEL - 133 ml Bottle Carton

sunmark®

COMPARE TO FLEET®
MINERAL OIL ENEMA
ACTIVE INGREDIENT*

NDC 49348-185-20

complete
ready-to-use

enema

Mineral Oil

Sodium free lubricant
laxative for relief of
occasional constipation

Comfortable,
lubricated tip

Works in minutes

NOT MADE WITH
NATURAL RUBBER
LATEX

4.5 FL OZ
(133 ml)